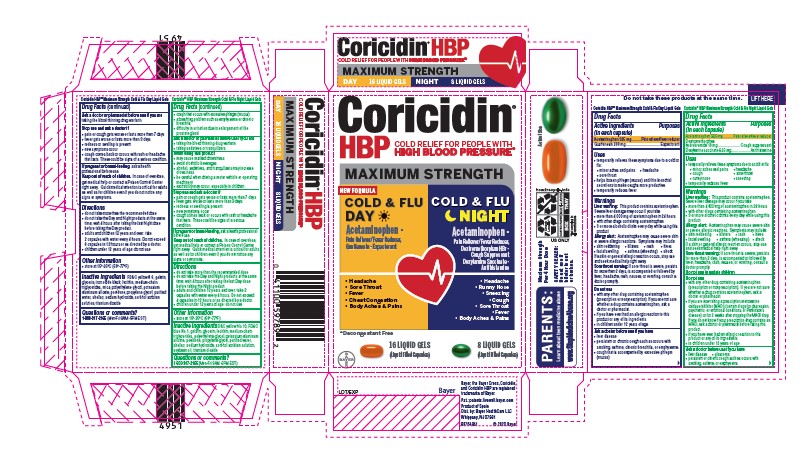 DRUG LABEL: Coricidin HBP Maximum Strength Cold and Flu Day and Night
NDC: 11523-0100 | Form: KIT | Route: ORAL
Manufacturer: Bayer HealthCare LLC.
Category: otc | Type: HUMAN OTC DRUG LABEL
Date: 20251204

ACTIVE INGREDIENTS: ACETAMINOPHEN 325 mg/1 1; GUAIFENESIN 200 mg/1 1; DOXYLAMINE SUCCINATE 6.25 mg/1 1; ACETAMINOPHEN 325 mg/1 1; DEXTROMETHORPHAN HYDROBROMIDE 10 mg/1 1
INACTIVE INGREDIENTS: MICA; LECITHIN, SOYBEAN; SHELLAC; SORBITOL; TITANIUM DIOXIDE; WATER; SODIUM HYDROXIDE; SORBITAN; FERROSOFERRIC OXIDE; POTASSIUM ALUMINUM DISILICATE; POVIDONE; FD&C YELLOW NO. 6; MEDIUM-CHAIN TRIGLYCERIDES; PROPYLENE GLYCOL; POLYETHYLENE GLYCOL, UNSPECIFIED; GELATIN; GLYCERIN; LECITHIN, SOYBEAN; SHELLAC; SORBITAN; MEDIUM-CHAIN TRIGLYCERIDES; POVIDONE; SODIUM HYDROXIDE; SORBITOL; SOYBEAN OIL; TITANIUM DIOXIDE; PROPYLENE GLYCOL; WATER; FD&C BLUE NO. 1; POLYETHYLENE GLYCOL, UNSPECIFIED; D&C YELLOW NO. 10; GELATIN; GLYCERIN

Coricidin HBP Maximum Strength Cold & Flu Day & Night Liquidgels

Coricidin HBP® Maximum Strength Cold & Flu Day Liquid Gels

Active ingredients

Active ingredients (in each capsule) Purposes

Acetaminophen 325 mg…………….………..Pain reliever/fever reducer

Guaifenesin 200 mg…………………………………………...Expectorant

Uses

· temporarily relieves these symptoms due to a cold or flu:

· minor aches and pains · headache

· sore throat

· helps loosen phlegm (mucus) and thin bronchial secretions to make

coughs more productive

· temporarily reduces fever

Warnings

Liver warning: This product contains acetaminophen. Severe liver damage may occur if you take

· more than 4,000 mg of acetaminophen in 24 hours

· with other drugs containing acetaminophen

· 3 or more alcoholic drinks every day while using this product

Allergy alert: Acetaminophen may cause severe skin or severe

allergic reactions. Symptoms may include:

· skin reddening · blisters · rash · hives

· facial swelling · asthma (wheezing) · shock

If a skin or general allergic reaction occurs, stop use and seek medical help right away.

Sore throat warning: If sore throat is severe, persists for more than

2 days, is accompanied or followed by fever, headache, rash, nausea,

or vomiting, consult a doctor promptly.

Do not use

● with any other drug containing acetaminophen (prescription or

nonprescription). If you are not sure whether a drug contains

acetaminophen, ask a doctor or pharmacist

● if you have ever had an allergic reaction to this product or any of its

ingredients

● in children under 12 years of age

Aska a doctor

Ask a doctor before use if you have

● liver disease

● persistent or chronic cough such as occurs with smoking, asthma,chronic bronchitis,

or emphysema

● cough that occurs with excess phelgm

Ask a doctor or pharmacist before use if you are taking the blood thinning drug warfarin

Stop use

Stop use and ask a doctor if

· pain or cough gets worse or lasts more than 7 days

· fever gets worse or lasts more than 3 days

· redness or swelling is present

· new symptoms occur

· cough comes back or occurs with rash or headache that lasts. These could be signs of a serious condition.

If pregnant or breast-feeding, ask a health professional before use.

Keep out of reach of children. In case of overdose, get medical help or contact a Poison Control Center right away. Quick medical attention is critical for adults as well as for children even if you do not notice any signs or symptoms.

Directions

· do not take more than the recommended dose

· do not take the Day and Night products at the same time; wait 4

hours after taking the last Night dose before taking the Day product.

· adults and children 12 years and over: take 2 capsules with water

every 4 hours. Do not exceed 6 capsules in 12 hours or as

directed by a doctor.

· children under 12 years of age: do not use

Other information

· store at 15º-25ºC (59º-77ºF)

Inactive ingrediens

Inactive ingredientsFD&C Yellow#6, gelatin, glycerin, iron oxide black, lecithin, medium-chain triglycerides, mica, polyethylene glycol, potassium aluminum silicate, povidone, propylene glycol, purified water, shellac, sodium hydroxide, sorbitol sorbitan solution, titanium dioxide

Questions or comments? 1-800-317-2165 (Mon-Fri 9AM -5PM EST)

Active ingredients (in each capsule)Purposes

Acetaminophen 325 mg…………….………...Pain reliever/fever reducer

Dextromethorphan hydrobromide 10 mg……………Cough suppressant

Doxylamine succinate 6.25 mg……………………………...Antihistamine

USES

- temporarily relieves these symptoms due to a cold or flu:
- minor aches and pains · headache · cough
- sore throat · runny nose · sneezing
- temporarily reduces fever

Liver Warning

Liver warning: This product contains acetaminophen. Severe liver damage may occur if you take

· more than 4,000 mg of acetaminophen in 24 hours

· with other drugs containing acetaminophen

· 3 or more alcoholic drinks every day while using this product

Allergy alert: Acetaminophen may cause severe skin or severe

allergic reactions. Symptoms may include:

· skin reddening · blisters · rash · hives

· facial swelling · asthma (wheezing) · shock

If a skin or general allergic reaction occurs, stop use and seek medical help right away.

Sore throat warning: If sore throat is severe, persists for more than

2 days, is accompanied or followed by fever, headache, rash, nausea,

or vomiting, consult a doctor promptly.

Do not use to sedate children

Do not use

● with any other drug containing acetaminophen (prescription or

nonprescription). If you are not sure whether a drug contains

acetaminophen, ask a doctor or pharmacist.

● if you are now taking a prescription monoamine oxidase inhibitor

(MAOI) (certain drugs for depression, psychiatric, or emotional

conditions, or Parkinson's disease), or for 2 weeks after stopping

the MAOI drug. If you do not know if your prescription drug contains

an MAOI, ask a doctor or pharmacist before taking this product.

● if you have ever had an allergic reaction to this product or any of its

ingredients

● in children under 12 years of age

Ask a doctor before use if you have

● liver disease ● glaucoma

● persistent or chronic cough such as occurs with smoking, asthma,

or emphysema

● cough that occurs with excessive phlegm (mucus)

● a breathing problem such as emphysema or chronic bronchitis

● difficulty in urination due to enlargement of the prostate gland

Ask a doctor or pharmacist before use if you are
● taking the blood thinning drug warfarin
● taking sedatives or tranquilizers

When using this product
● may cause marked drowsiness
● avoid alcoholic beverages
● alcohol, sedatives, and tranquilizers may increase drowsiness
● be careful when driving a motor vehicle or operating machinery
● excitability may occur, especially in children

Stop use and ask a doctor if

· pain or cough gets worse or lasts more than 7 days

· fever gets worse or lasts more than 3 days

· redness or swelling is present

· new symptoms occur

· cough comes back or occurs with rash or headache that lasts. These could be signs of a serious condition

PREGNANCY OR BREAST FEEDING

If pregnant or breast-feeding, ask a health professional before use.

Keep out of reach of children. In case of overdose, get medical help or contact a Poison Control Center right away. Quick medical attention is critical for adults as well as for children even if you do not notice any signs or symptoms.

Directions

· do not take more than the recommended dose

· do not take the Day and Night products at the same time; wait 4

hours after taking the last Day dose before taking the Night product.

· adults and children 12 years and over: take 2 capsules with water

every 4 hours. Do not exceed 4 capsules in 12 hours or as

directed by a doctor.

· children under 12 years of age: do not use

Other information

· store at 15º-25ºC (59º-77ºF)

INACTIVE INGREDIENT

Inactive ingredients D&C yellow No.10, FD&C blue No.1, gelatin, glycerin, lecithin, medium-chain triglycerides, silica, polyethylene glycol, potassium aluminum silicate, povidone, propylene glycol, purified water, shellac, sodium hydroxide, sorbitol sorbitan solution, soybean oil, titanium dioxide

Questions or comments?1-800-317-2165 (Mon-Fri 9AM -5PM EST)

Coricidin® HBP Maximum Strength Cold & Flu Liquid Gels

PACKAGE LABEL

Coricidin® HBP

COLD RELIEF FOR PEOPLE WITH HIGH BLOOD PRESSUREƗ

MAXIMUM STRENGTH

COLD & FLU DAY

ACETAMINOPHEN - Pain Reliever/Fever Reducer

GUAIFENESIN - Expectorant

Relieves

- Body Aches & Pains
- Headache
- Chest Congestion
- Sore Throat
- Fever

Ɨ Decongestant Free

16 LIQUID GELS

(Liquid Filled Capsules)

COLD & FLU NIGHT

DOXYLAMINE SUCCINATE - Antihistamine

ACETAMINOPHEN - Pain Reliever/Fever Reducer

DEXTROMETHORPHAN HBr- Cough Suppressant

RELIEVES

- Body Aches & Pains
- Headache
- Runny Nose & Sneezing
- Cough
- Sore Throat
- Fever

Ɨ Decongestant Free

8 LIQUID GELS

(Liquid Filled Capsules)